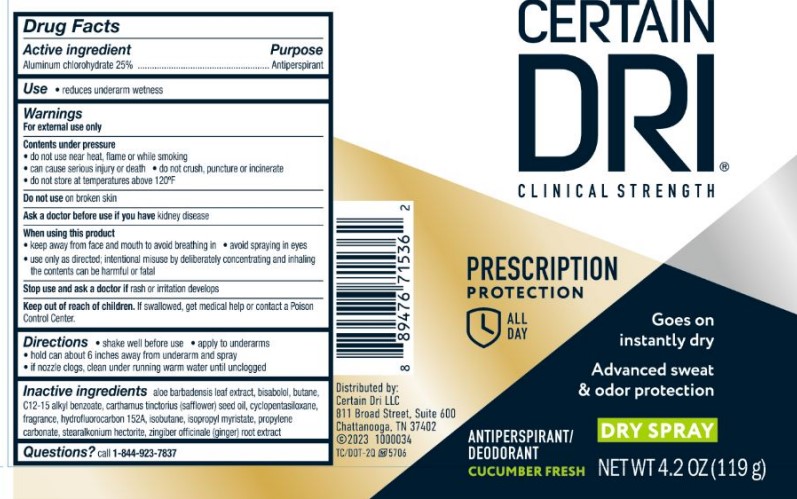 DRUG LABEL: Certain Dri Cucumber Fresh
NDC: 69693-721 | Form: SPRAY
Manufacturer: Clarion Brands, LLC
Category: otc | Type: HUMAN OTC DRUG LABEL
Date: 20251223

ACTIVE INGREDIENTS: ALUMINUM CHLOROHYDRATE 25 g/100 g
INACTIVE INGREDIENTS: ALOE VERA LEAF; LEVOMENOL; BUTANE; ALKYL (C12-15) BENZOATE; SAFFLOWER OIL; CYCLOMETHICONE 5; 1,1-DIFLUOROETHANE; ISOBUTANE; ISOPROPYL MYRISTATE; PROPYLENE CARBONATE; STEARALKONIUM HECTORITE; GINGER

Drug Facts

Active ingredient | Purpose
Aluminum chlorohydrate 25% | Antiperspirant

Use

- reduces underarm wetness

Warnings For external use only

Contents under pressure

- do not use near heat, flame or while smoking
- can cause serious injury or death
- do not crush, puncture or incinerate
- do not store at temperatures above 120ºF

Do not useon broken skin

Ask a doctor before use if you havekidney disease

When using this product

- keep away from face and mouth to avoid breathing in
- avoid spraying in eyes
- use only as directed; intentional misuse by deliberately concentrating and inhaling the contents can be harmful or fatal

Stop use and ask a doctorif rash or irritation develops

Keep out of reach of children. If swallowed, get medical help or contact a Poison Control Center.

Directions

- shake well before use
- apply to underarms
- hold can about 6 inches away from underarm and spray
- if nozzle clogs, clean under running warm water until unclogged

Inactive ingredients

aloe barbadensis leaf extract, bisabolol, butane, C12-15 alkyl benzoate, carthamus tinctorius (safflower) seed oil, cyclopentasiloxane, fragrance, hydrofluorocarbon 152A, isobutane, isopropyl myristate, propylene carbonate, stearalkonium hectorite, zingiber officinale (ginger) root extract

Questions?call 1-844-923-7837

PRINCIPAL DISPLAY PANEL

CERTAIN
DRI®
CLINICAL STRENGTH
PRESCRIPTION
PROTECTION
ALL
DAY
Goes on
instantly dry
Advanced sweat
& odor protection
ANTIPERSPIRANT/
DEODORANT
DRY SPRAY
CUCUMBER FRESH
NET WT 4.2 OZ (119 g)
Distributed by:
Certain Dri LLC
8111 Broad Street, Suite 600
Chattanooga, TN 37402
©2023 1000034